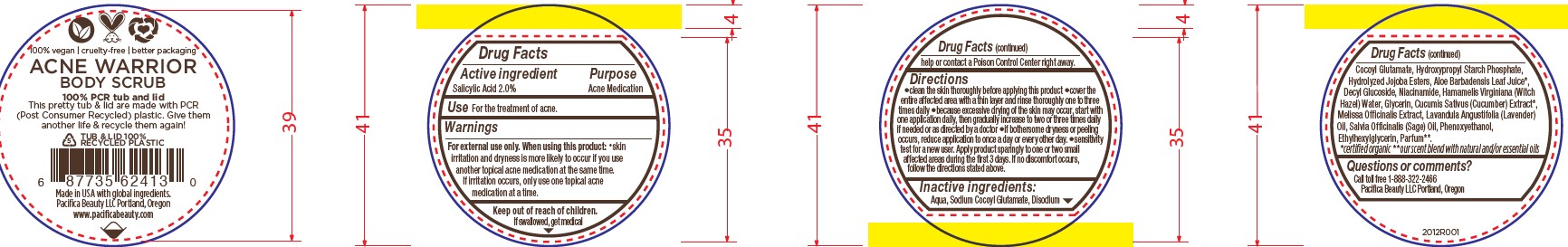 DRUG LABEL: Acne Warrior Body Scrub
NDC: 61197-410 | Form: CREAM
Manufacturer: Pacifica Beauty, LLC
Category: otc | Type: HUMAN OTC DRUG LABEL
Date: 20250103

ACTIVE INGREDIENTS: SALICYLIC ACID 2 g/100 g
INACTIVE INGREDIENTS: WATER; HAMAMELIS VIRGINIANA LEAF WATER; SODIUM COCOYL GLUTAMATE; NIACINAMIDE; MELISSA OFFICINALIS; SALVIA OFFICINALIS WHOLE; ETHYLHEXYLGLYCERIN; ALOE VERA LEAF; DECYL GLUCOSIDE; PHENOXYETHANOL; CUCUMIS SATIVUS WHOLE; HYDROLYZED JOJOBA ESTERS (ACID FORM); GLYCERIN; LAVANDULA ANGUSTIFOLIA WHOLE; DISODIUM COCOYL GLUTAMATE

Acne Warrior Body Scrub

Active ingredient Purpose

Salicylic Acid 2.0% Acne Medication

Use

For the treatment of acne.

Warnings

For external use only. When using this product: skin irritation and dryness is more likely to occur if you use another topical acne medication at the same time. If irritation occurs, only use one topical acne medication at a time.

When using this product: skin irritation and dryness is more likely to occur if you use another topical acne medication at the same time. If irritation occurs, only use one topical acne medication at a time.

Keep out of reach of children.

If swallowed, get medical help or contact a Poison Control Center right away.

Directions

Clean the skin thoroughly before applying this product. Cover the entire affected area with a thin layer and rinse thoroughly one to three times daily. Because excessive drying of the skin may occur, start with one application daily, then gradually increase to two or three times daily if needed or as directed by a doctor. If bothersome dryness or peeling occurs, reduce application to once a day or every other day. Sensitivity test for a new user. Apply product sparingly to one or two small affected areas during the first 3 days. If no discomfort occurs, follow the directions stated above.

Inactive ingredients:

Aqua, Sodium Cocoyl Glutamate, Disodium Cocoyl Glutamate, Hydroxypropyl Starch Phosphate, Hydrolyzed Jojoba Esters, Aloe Barbadensis Leaf Juice*, Decyl Glucoside, Niacinamide, Hamamelis Virginiana (Witch Hazel) Water, Glycerin, Cucumis Sativus (Cucumber) Extract*, Melissa Officinalis Extract, Lavandula Angustifolia (Lavender) Oil, Salvia Officinalis (Sage) Oil, Phenoxyethanol, Ethylhexylglycerin, Parfum**.

*certified organic **our sent blend with natural and/or essetial oils

Questions or comments?

Call toll free 1-888-322-2466
Pacifica Beauty LLC Portland, Oregon